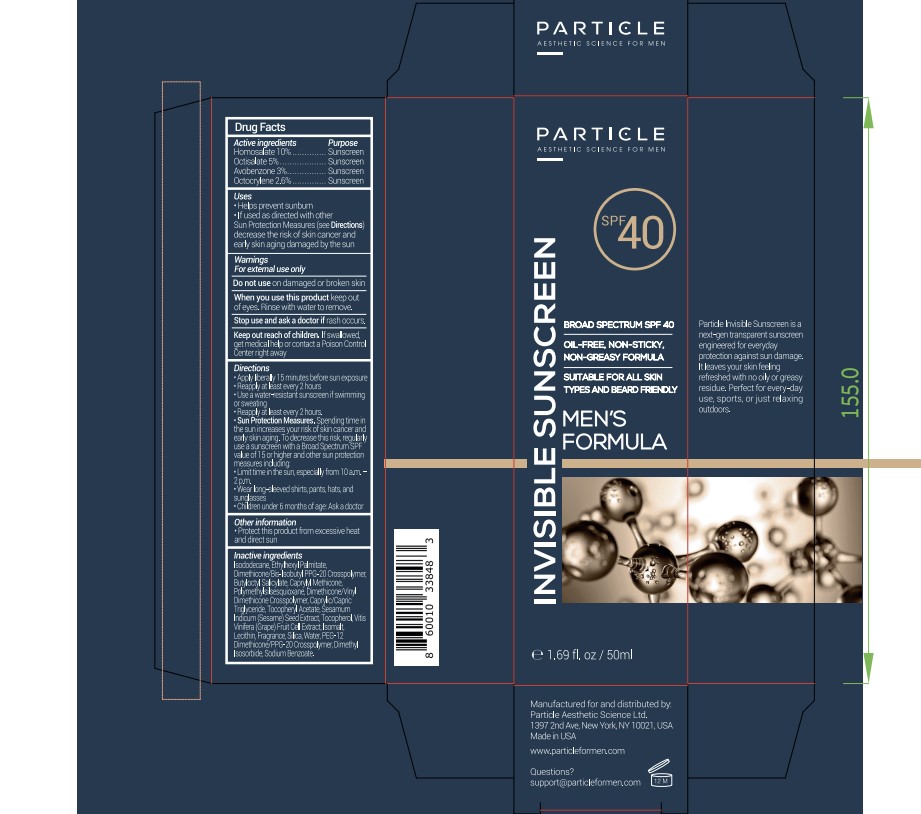 DRUG LABEL: Invisible Sunscreen SPF 40
NDC: 84426-001 | Form: CREAM
Manufacturer: PARTICLE AESTHETIC SCIENCE LTD
Category: otc | Type: HUMAN OTC DRUG LABEL
Date: 20251119

ACTIVE INGREDIENTS: HOMOSALATE 10 mg/100 mg; OCTISALATE 5 mg/100 mg; OCTOCRYLENE 2.6 mg/100 mg; AVOBENZONE 3 mg/100 mg
INACTIVE INGREDIENTS: DIMETHICONE/VINYL DIMETHICONE CROSSPOLYMER (SOFT PARTICLE); SODIUM BENZOATE; PEG-12 DIMETHICONE/PPG-20 CROSSPOLYMER; DIMETHYL ISOSORBIDE; ISOMALT; CAPRYLYL TRISILOXANE; POLYMETHYLSILSESQUIOXANE (4.5 MICRONS); TOCOPHEROL; ISODODECANE; BUTYLOCTYL SALICYLATE; MEDIUM-CHAIN TRIGLYCERIDES; LECITHIN, SUNFLOWER; SILICON DIOXIDE; DIMETHICONE/BIS-ISOBUTYL PPG-20 CROSSPOLYMER; SESAME SEED; VITIS VINIFERA FRUIT RIND; WATER; ETHYLHEXYL PALMITATE; .ALPHA.-TOCOPHEROL ACETATE

PARTICLE FOR MEN INVISIBLE SUNSCREEN SPF 40

Active ingredients

Homosalate 10%

Octisalate 5%

Avobenzone 3%

Octocrylene 2.6%

Purpose

Sunscreen

Uses

- Helps prevent sunburn
- If used as directed with other Sun Protection Measures (see Directions) decrease the risk of skin cancer and early skin aging damaged by the sun

Warnings

For external use only

Do not useon damaged or broken skin

WHEN USING

When you use this productkeep out of eyes. Rinse with water to remove

Stop use and ask a doctor ifrash occurs

Keep out of reach of children.If swallowed, get medical help or contact a Poison Control Center right away.

Directions

- Apply liberally 15 minutes before sun exposure
- Reapply at least every 2 hours
- Use a water-resistant sunscreen if swimming or sweating
- Reapply at least every 2 hours
- Sun Protection Measures.Spending time in the sun increases your risk of skin cancer and early skin aging. To decrease this risk, regularly use a sunscreen with a Broad Spectrum SPF value of 15 or higher and other sun protection measures including
- Limit time in the sun, especially from 10 a.m. - 2 p.m.
- Wear long-sleeved shirts, pants, hats, and sunglasses
- Children under 6 months of age: Ask a doctor

Other information

- Protect this product from excessive heat and direct sun

Inactive Ingredients:

Isodecane, Ethylhexyl Pamitate, Dimethicone/Bis-Isobutyl PPG-20 Crosspolymer, Butyloctyl Salicylate, Caprylyl Methicone, Polymethylsislsesquioxane, Dimethicone/Vinyl Dimethicone Crosspolymer, Caprylic/Capric Triglyceride, Tocopheryl Acetate, Sesamum Indicum(Sesame) Seed Extract, Tocopherol, Vitis Vinifera (Grape) Fruit Cell Extract, Isomalt, Lecithin, Fragrance, Silica, Water, PEG-12 Dimethicone/PPG-20 Crosspolymer, Dimethyl Isosorbide, Sodium Benzoate